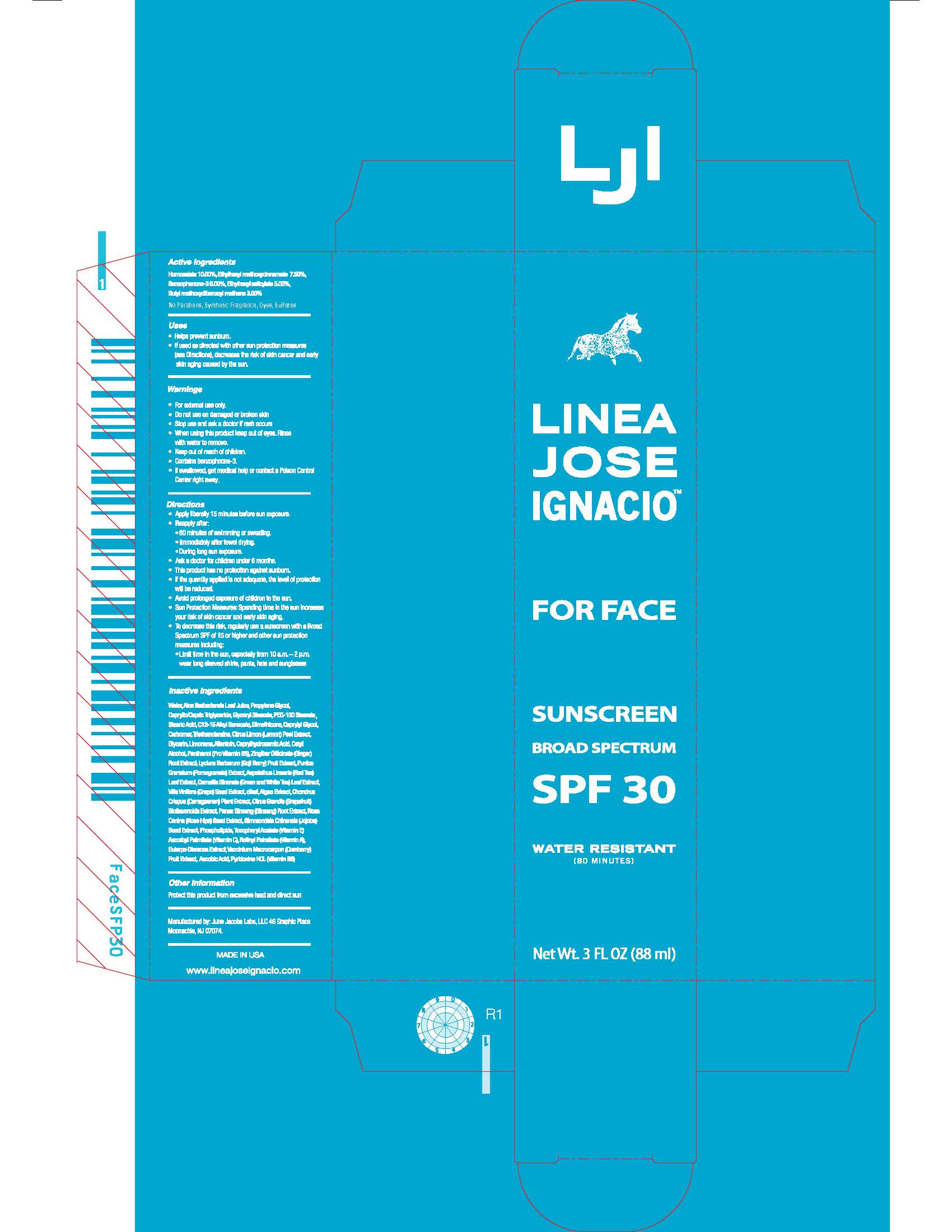 DRUG LABEL: Linea Jose Ignacio For Face Sunscreen Broad Spectrum SPF 30
NDC: 69096-8001 | Form: LOTION
Manufacturer: Linea Jose Ignacio LLC
Category: otc | Type: HUMAN OTC DRUG LABEL
Date: 20180901

ACTIVE INGREDIENTS: OXYBENZONE 5.3032 g/88.3872 g; OCTINOXATE 6.629 g/88.3872 g; AVOBENZONE 2.6516 g/88.3872 g; HOMOSALATE 8.8387 g/88.3872 g; OCTISALATE 4.4193 g/88.3872 g
INACTIVE INGREDIENTS: CARBOMER 940; PROPYLENE GLYCOL; VITIS VINIFERA SEED; PUNICA GRANATUM ROOT BARK; LEMON PEEL; LYCIUM BARBARUM ROOT BARK; DIMETHICONE; CETYL ALCOHOL; TROLAMINE; ALKYL (C12-15) BENZOATE; ASPALATHUS LINEARIS LEAF; PEG-100 STEARATE; CAPRYLYL GLYCOL; STEARIC ACID; MEDIUM-CHAIN TRIGLYCERIDES; GLYCERYL STEARATE SE; GLYCERIN; CAPRYLHYDROXAMIC ACID; GREEN TEA LEAF; PANTHENOL; WATER; ALOE VERA LEAF; LIMONENE, (+)-; ALLANTOIN; ZINGIBER OFFICINALE WHOLE

For Face Sunscreen Broad Spectrum SPF 30

Linea Jose Ignacio For Face Sunscreen Broad Spectrum SPF 30

Drug Facts

Active Ingredients

Homosalate 10.00%
Ethylhexyl methoxycinnamate 7.50%
Benzophenone-3 6.00%
Ethylhexyl salicylate 5.00%
Butyl methoxydibenzoyl methane 3.00%

Uses

- Helps prevent sunburn.
- If used as directed with other sun protection measures (see Directions), decreases the risk of skin cancer and early skin aging caused by the sun.

Warnings

- For external use only.
- Do not use on damaged or broken skin
- Stop use and ask a doctor if rash occurs
- When using this product keep out of eyes. Rinse with water to remove.
- Keep out of reach of children.
- Contains benzophnone-3.
- If swallowed, get medical help or contact a Poison Control Center right away.

Directions

- Apply liberally 15 minutes before sun exposure.
- Reapply after:

* 80 minutes of swimming or sweating.

* Immediately after towel drying.

* During long sun exposure.

- Ask a doctor for children under 6 months.
- This product has no protection against sunburn.
- If the quantity applied is not adequate, the level of protection will be reduced.
- Avoid prolonged exposure of children to the sun.
- Sun Protection Measures: Spending time in the sun increases you risk of skin cancer and early skin aging.
- To decrease this risk, regularly use a sunscreen with a Broad Spectrum SPF of 15 or higher and other sun protection measures including:

*Limit time in the sun, especially from 10 a.m. – 2 p.m. wear long sleeved shirts, pants, hats and sunglasses.

Inactive Ingredients

Water/Aqua/Eau, Aloe Barbadensis Leaf Juice, Propylene Glycol, Caprylic/Capric Triglyceride, Glyceryl Stearate, PEG-100 Stearate, Stearic Acid, C12-15 Alkyl Benzoate, Dimethicone, Caprylyl Glycol, Carbomer, Triethanolamine, Citrus Limon (Lemon) Peel Extract, Glycerin, Limonene, Allantoin, Caprylhydroxamic Acid, Cetyl Alcohol, Panthenol (Pro Vitamin B5), Zingiber Officinale (Ginger) Root Extract, Lycium Barbarum (Goji Berry) Fruit Extract, Punica Granatum (Pomegranate) Extract, Aspalathus Linearis (Red Tea) Leaf Extract, Camellia Sinensis (Green and White Tea) Leaf Extract, Vitis Vinifera (Grape) Seed Extract

Other Information

Protect this product from excessive heat and direct sun

Questions or comments

www.lineajoseignacio.com